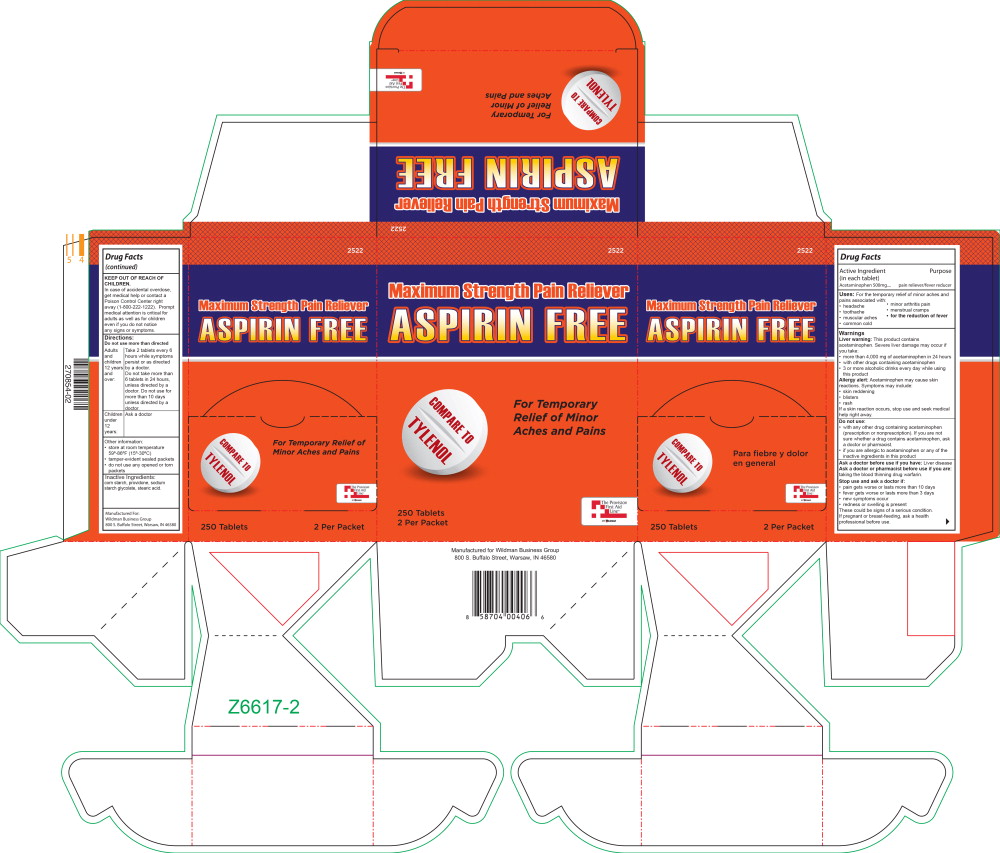 DRUG LABEL: Acetaminophen
NDC: 84269-2522 | Form: TABLET
Manufacturer: Wildman Business Group
Category: otc | Type: HUMAN OTC DRUG LABEL
Date: 20240520

ACTIVE INGREDIENTS: Acetaminophen 500 mg/1 1
INACTIVE INGREDIENTS: STARCH, CORN; POVIDONE, UNSPECIFIED; SODIUM STARCH GLYCOLATE TYPE A POTATO; STEARIC ACID

Drug Facts

Active Ingredient (in each tablet)

Acetaminophen

Purpose

Pain reliever / fever reducer

Uses:

For the temporary relief of minor aches and pains associated with:

- headache
- toothache
- muscular aches
- common cold
- minor arthritis pain
- menstrual cramps
- For the reduction of fever

Warnings

Liver warning: This product contains acetaminophen. Severe liver damage may occur if you take:

- more than 4,000 mg of acetaminophen in 24 hours
- with other drugs containing acetaminophen
- 3 or more alcoholic drinks every day while using this product

Allergy alert: Acetaminophen may cause skin reactions. Symptoms may include:

- skin reddening
- blisters
- rash

If a skin reaction occurs, stop use and seek medical help right away.

Do not use:

- with any other drug containing acetaminophen (prescription or nonprescription). If you are not sure whether a drug contains acetaminophen, ask a doctor or pharmacist.
- if you are allergic to acetaminophen or any of the inactive ingredients in this product

Ask a doctor before use if you have:

- Liver disease

Ask a doctor or pharmacist before us if you are:

- taking the blood thinning drug warfarin

Stop use and ask a doctor if:

- pain gets worse or lasts more than 10 days
- fever gets worse or lasts more than 3 days
- new symptoms occur
- redness or swelling is present

These could be signs of a serious condition.

PREGNANCY OR BREAST FEEDING

If pregnant or breast-feeding, ask a health professional before use.

Keep out of reach of children.

In case of accidental overdose, get medical help or contact a Poison Control Center right away (1-800-222-1222). Prompt medical attention is critical for adults as well as for children even if you do not notice any signs or symptoms.

Directions:

Do not use more than directed

Adults and children 12 years and over

- take 2 tablets every 6 hours while symptoms persist or as directed by a doctor.
- do not take more than 6 tablets in 24 hours, unless directed by a doctor
- do not use for more than 10 days unless directed by a doctor

Children under 12 years: Ask a doctor

Other information:

- store at room temperature 59º-86ºF (15º-30ºC)
- tamper-evident sealed packets
- do not use any opened or torn packets

Inactive Ingredients

Corn starch, unspecified povidone, sodium starch glycolate, stearic acid

Principal Display Panel – 250 Tablet Box Label

2522

Maximum Strength Pain Reliever

ASPIRIN FREE

COMPARE TO
TYLENOL

For Temporary
Relief of Minor
Aches and Pains

250 tablets

2 Per Packet

The Provision
First Aid
Line™

BY WILDMAN